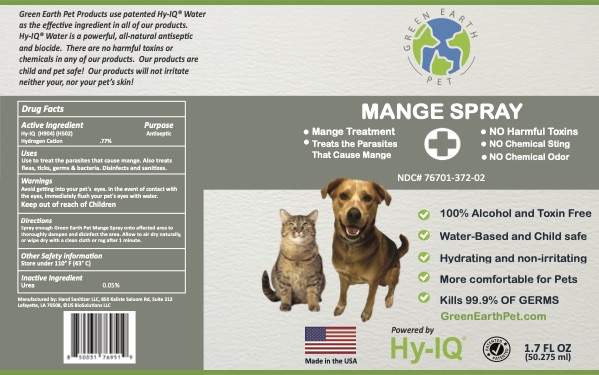 DRUG LABEL: Green Earth Pet Mange
NDC: 76701-372 | Form: SPRAY
Manufacturer: HAND SANITIZER LLC
Category: animal | Type: OTC ANIMAL DRUG LABEL
Date: 20210813

ACTIVE INGREDIENTS: HYDROGEN CATION 10 mg/1 mL
INACTIVE INGREDIENTS: WATER 940 mg/1 mL; UREA 50 mg/1 mL

Green Earth Pet Mange

Active Ingredient

Hy-IQ (H904) (H502)
Hydrogen Cation .77%

Purpose

Antiseptic

Uses

Use to treat the parasites that cause mange. Also treats fleas, ticks, germs, and bacteria. Disinfects and sanitizes.

Warnings

Avoid getting into your pet's eyes. In the event of contact with the eyes, immediately flush your pet's eyes with water.

Keep Out of Reach of Children

Directions

Spray enough Green Earth Pet Mange Spray onto affected area to thoroughly dampen and disinfect the area. Allow to air dry naturally, or wipe dry with a clean cloth or rag after one minute.

Other Safety Information

Store under 110º F (43º C)

Inactive Ingredients

Water, Urea

Green Earth Pet Mange Spray